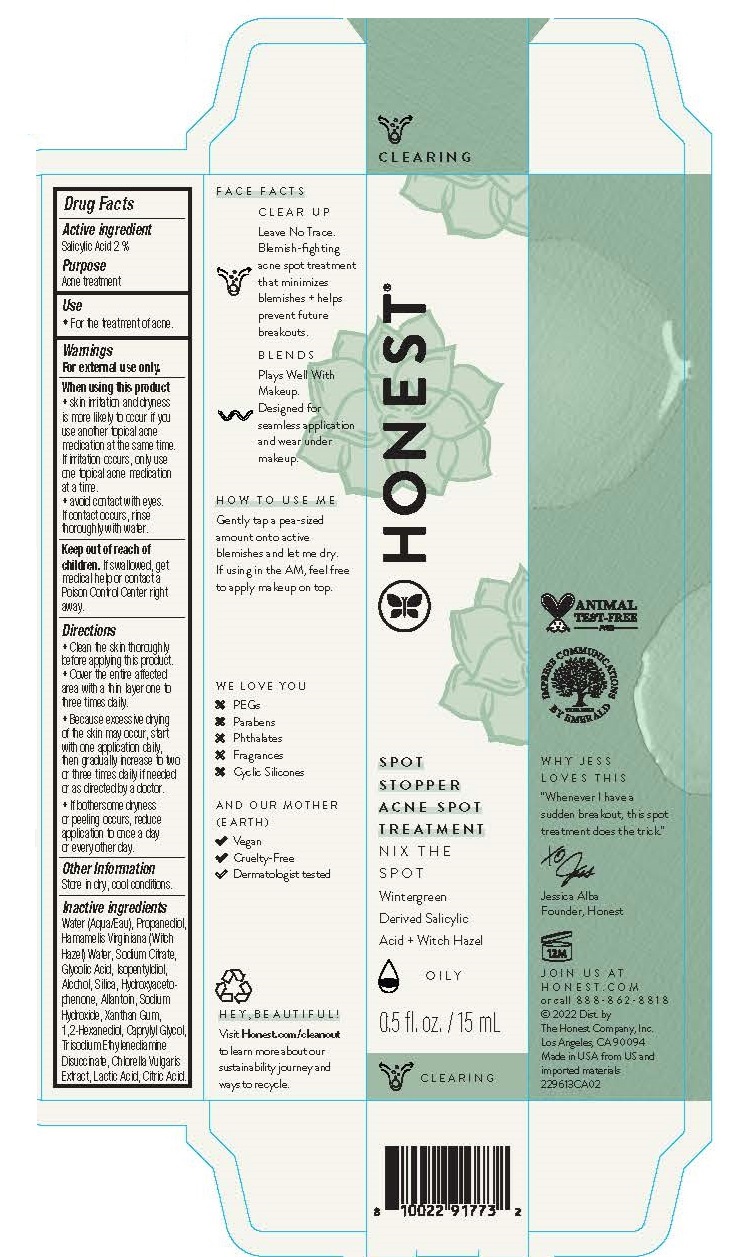 DRUG LABEL: Spot Stopper Acne Spot Treatment
NDC: 69366-412 | Form: GEL
Manufacturer: The Honest Company, Inc
Category: otc | Type: HUMAN OTC DRUG LABEL
Date: 20231219

ACTIVE INGREDIENTS: SALICYLIC ACID 2 g/100 mL
INACTIVE INGREDIENTS: PROPANEDIOL; HAMAMELIS VIRGINIANA TOP WATER; SODIUM CITRATE; GLYCOLIC ACID; ISOPENTYLDIOL; ALCOHOL; SILICON DIOXIDE; WATER; 1,2-HEXANEDIOL; CAPRYLYL GLYCOL; HYDROXYACETOPHENONE; ALLANTOIN; SODIUM HYDROXIDE; XANTHAN GUM; TRISODIUM ETHYLENEDIAMINE DISUCCINATE; ANHYDROUS CITRIC ACID; CHLORELLA VULGARIS; LACTIC ACID

Spot Stopper Acne Spot Treatment

Active ingredientSalicylic Acid 2%

PURPOSE

PurposeAcne treatment

INDICATIONS AND USAGE

Use♦ For the treatment of acne.

Warnings

For external use only.

When using this product

♦ skin irritation and dryness is more likely to occur if you use another topical acne medication at the same time. If irritation occurs, only use one topical acne medication at a time.

♦ avoid contact with eyes. If contact occurs, rinse thoroughly with water.

Keep out of reach of children. If swallowed, get medical help or contact a Poison Control Center right away.

Directions

♦ Clean the skin thoroughly before applying this product.

♦ Cover the entire affected area with a thin layer one to three times daily.

♦ Because excessive drying of the skin may occur, start with one application daily, then gradually increase to two or three times daily if needed or as directed by a doctor.

♦ If bothersome dryness or peeling occurs, reduce application to once a day or every other day.

Other information

Store in dry, cool conditions.

Inactive ingredients

Water (Aqua/Eau), Propanediol, Hamamelis Virginiana (Witch Hazel) Water, Sodium Citrate, Glycolic Acid, Isopentyldiol, Alcohol, Silica, Hydroxyaceto-phenone, Allantoin, Sodium Hydroxide, Xanthan Gum, 1,2-Hexanediol, Caprylyl Glycol, Trisodium Ethylenediamine Disuccinate, Chlorella Vulgaris Extract, Lactic Acid, Citric Acid.

HOW TO USE ME

Gently tap a pea-sized amount onto active blemishes and let me dry. If using in the AM, feel free to apply makeup on top.

PACKAGE LABEL

HONEST®

SPOT STOPPER ACNE SPOT TREATMENT

NIX THE SPOT

Wintergreen Derived Salicylic Acid + Witch Hazel

0.5 fl. oz. / 15 mL

HONEST.COM

or call 888-862-8818

©2022 Dist. by

The Honest Company, Inc.

Los Angeles, CA 90094

Made in USA from US and imported materials